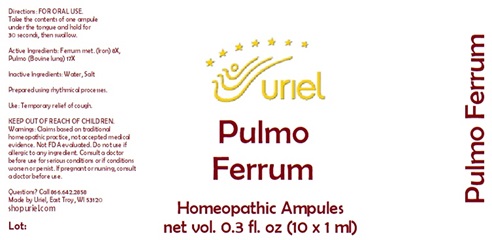 DRUG LABEL: Pulmo Ferrum
NDC: 48951-8087 | Form: LIQUID
Manufacturer: Uriel Pharmacy Inc.
Category: homeopathic | Type: HUMAN OTC DRUG LABEL
Date: 20251030

ACTIVE INGREDIENTS: SUS SCROFA LUNG 17 [hp_X]/1 mL; IRON 8 [hp_X]/1 mL
INACTIVE INGREDIENTS: WATER; SODIUM CHLORIDE; LACTOSE

Pulmo Ferrum

INDICATIONS AND USAGE

Directions: FOR ORAL USE.

DOSAGE AND ADMINISTRATION

Take the contents of one ampule under the tongue and hold for 30 seconds, then swallow.

ACTIVE INGREDIENT

Active Ingredients: Ferrum met. (Iron) 8X, Pulmo (Bovine lung) 17X

Inactive Ingredients: Water, Salt

Prepared using rhythmical processes.

PURPOSE

Use: Temporary relief of cough.

KEEP OUT OF REACH OF CHILDREN.

WARNINGS

Warnings: Claims based on traditional homeopathic practice, not accepted medical evidence. Not FDA evaluated. Do not use if allergic to any ingredient. Consult a doctor before use for serious conditions or if conditions worsen or persist. If pregnant or nursing, consult a doctor before use.

Questions? Call 866.642.2858
Made by Uriel, East Troy, WI 53120
shopuriel.com